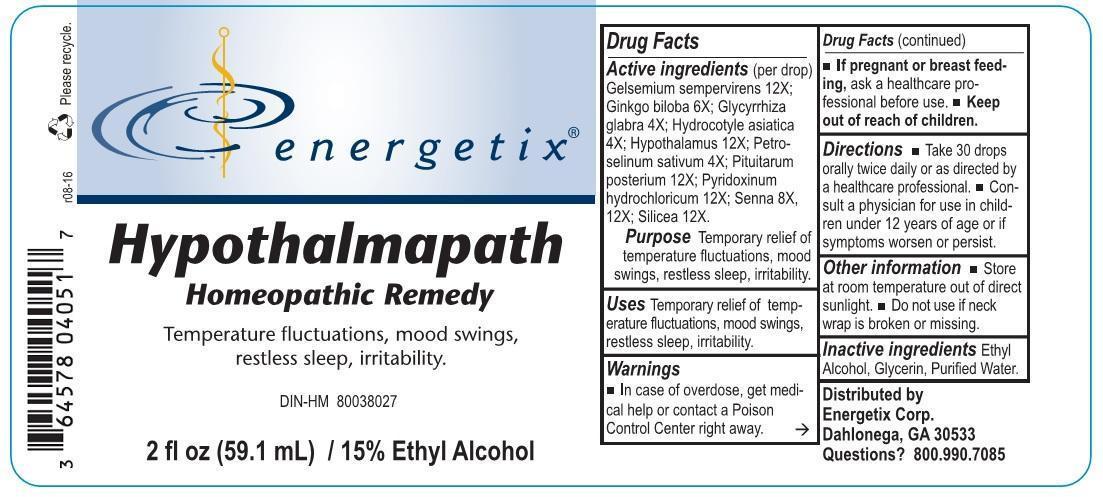 DRUG LABEL: Hypothalmapath
NDC: 64578-0124 | Form: LIQUID
Manufacturer: Energetix Corp
Category: homeopathic | Type: HUMAN PRESCRIPTION DRUG LABEL
Date: 20170103

ACTIVE INGREDIENTS: GELSEMIUM SEMPERVIRENS ROOT 12 [hp_X]/1 mL; GINKGO 6 [hp_X]/1 mL; GLYCYRRHIZA GLABRA 4 [hp_X]/1 mL; CENTELLA ASIATICA 4 [hp_X]/1 mL; BOS TAURUS HYPOTHALAMUS 12 [hp_X]/1 mL; PETROSELINUM CRISPUM 4 [hp_X]/1 mL; BOS TAURUS PITUITARY GLAND, POSTERIOR 12 [hp_X]/1 mL; PYRIDOXINE HYDROCHLORIDE 12 [hp_X]/1 mL; SENNA LEAF 8 [hp_X]/1 mL; SILICON DIOXIDE 12 [hp_X]/1 mL
INACTIVE INGREDIENTS: WATER; GLYCERIN; ALCOHOL

Drug Facts:

Active ingredient (per drop)

Gelsemium sempervirens 12X; Ginkgo biloba 6X; Glycyrrhiza glabra 4X; Hydrocotyle asiatica 4X; Hypothalamus 12X; Petroselinum sativum 4X; Pituitarum posterium 12X; Pyridoxinum hydrochloricum 12X; Senna 8X, 12X; Silicea 12X.

Purpose

Temporary relief of temperature fluctuations, mood swings, restless sleep, irritability.

Uses

Temporary relief of temperature fluctuations, mood swings, restless sleep, irritability.

Warnings

- In case of overdose, get medical help or contact a Poison Control Center right away.
- If pregnant or breast feeding, ask a health professional before use.
- Keep out of reach of children.

Keep out of reach of children.

Directions

- Take 30 drops orally twice daily or as directed by a healthcare professional.
- Consult a physician for use in children under 12 years of age or if symptoms worsen or persist.

Other information

- Store at room temperature out of direct sunlight.
- Do not use if neck wrap is broken or missing.

Inactive ingredients

Ethyl Alcohol, Glycerin, Purified Water.

QUESTIONS

Distributed by

Energetix Corp.

Dahlonega, GA 30533

Questions? 800.990.7085

PURPOSE

Temperature fluctuations, mood swings, restless sleep, irritability.

PACKAGE LABEL

energetix

Hypothalmapath

Homeopathic Remedy

Temperature fluctuations, mood swings,

restless sleep, irritability

DIN-HM 80038027

2 fl oz (59.1 mL) / 15% Ethyl Alcohol